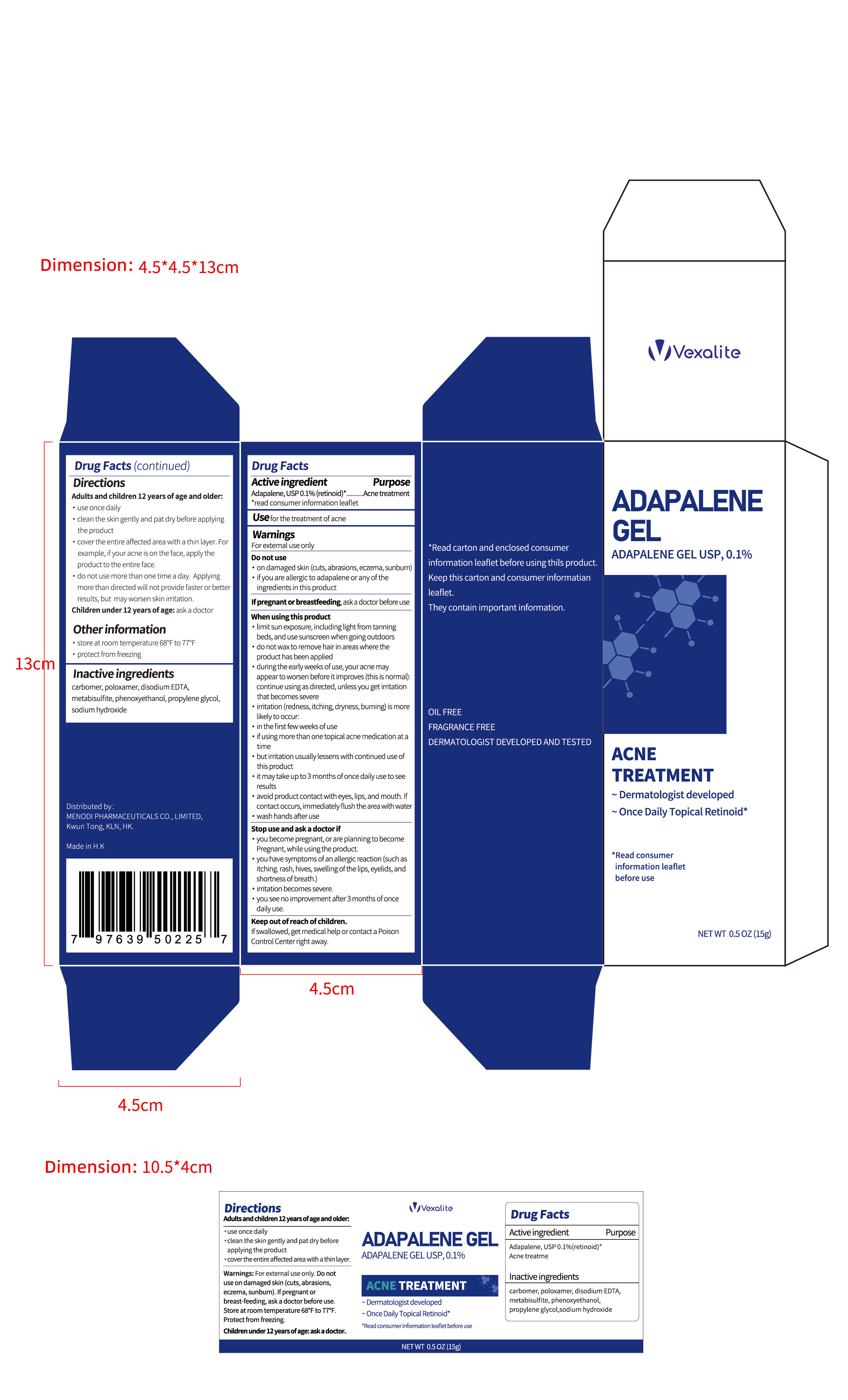 DRUG LABEL: ADAPALENE Gel
NDC: 84893-001 | Form: GEL
Manufacturer: Menodi Pharmaceuticals Co., Limited
Category: otc | Type: HUMAN OTC DRUG LABEL
Date: 20241106

ACTIVE INGREDIENTS: ADAPALENE 0.1 g/100 g
INACTIVE INGREDIENTS: SODIUM HYDROXIDE; CARBOMER; POLOXAMER 105; EDETATE DISODIUM; METABISULFITE ION; PHENOXYETHANOL; PROPYLENE GLYCOL

ADAPALENE GEL

ADAPALENE GEL

ACTIVE INGREDIENT

ADAPALENE 0.1%

PURPOSE

Acne treatment

INDICATIONS AND USAGE

Usefor the treatment of acne

WARNINGS

For external use only

DO NOT USE

on damaged skin (cuts,abrasions, eczema, sunburn)

if you are allergic to adapalene or any oftheingredients in this product

WHEN USING

limit sun exposure, including light from tanningbeds, and use sunscreen when goingoutdoors.
do not wax to remove hair in areas where theproduct has been applied.
during the early weeks of use, your acne mayappearto worsen before it improves (this is normal)continue using as directed, unless you get irritationthat becomes severe
irritation (redness, itching, dryness, burning) is morelikely to occur:
in the first few weeks of use.
if using more than one topical acne medication at atime
but irritation usually lessens with continued use of this product
it may take up to 3 months of once daily use to see results
avoid product contact with eyes, lips, and mouth. lfcontact occurs, immediatelyflush the area with waterwash hands after use

STOP USE

you become pregnant, or are planning to becomePregnant, while using the product.
you have symptoms of an allergic reaction (such asitching. rash, hives, swelling ofthe lips, eyelids, andshortness of breath.)
irritation becomes severe.
you see no improvement after3 months ofoncedaily use.

KEEP OUT OF REACH OF CHILDREN

If swallowed, get medical help or contact a PoisonControl Center right away.

DOSAGE AND ADMINISTRATION

Adults and children 12 years of age and older:
use once daily
clean the skin gently and pat dry before applyingthe product
cover the entire affected area with a thin layer. Forexample, if your acne is on the face, apply theproduct to the entire face.
do not use more than one time a day. Applyingmore than directed will not provide faster or betterresults, but may worsen skin irritation.Children under 12 years of age: ask a doctor

STORAGE AND HANDLING

store at room temperature 68°F to 77°F
protect from freezing

INACTIVE INGREDIENT

Carbomer
Poloxamer
Disodium EDTA
Metabisulfite
Phenoxyethanol
Propylene Glycol
Sodium Hydroxide